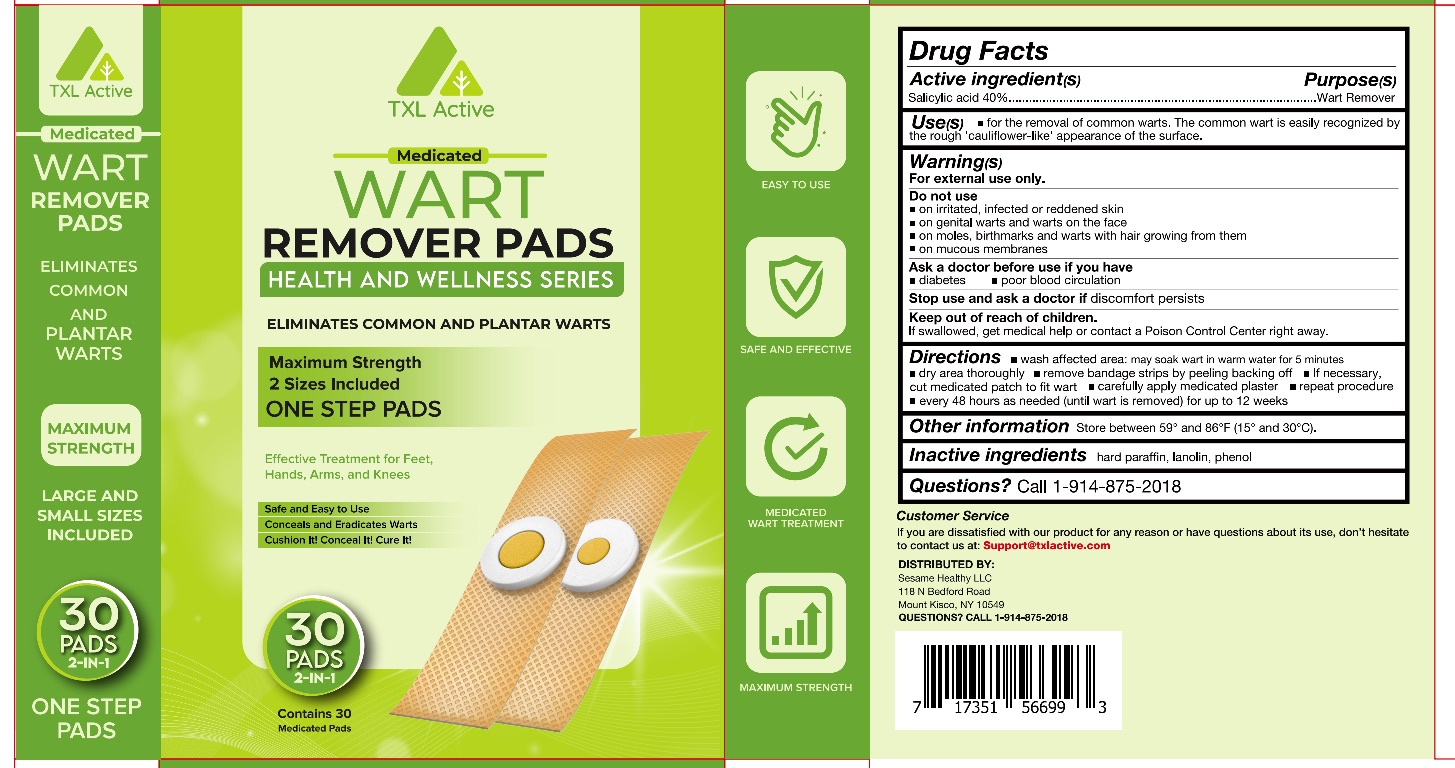 DRUG LABEL: TXL Active Wart Remover Pads
NDC: 83124-003 | Form: PATCH
Manufacturer: Kairos Trading Inc
Category: otc | Type: HUMAN OTC DRUG LABEL
Date: 20230517

ACTIVE INGREDIENTS: SALICYLIC ACID 40 g/100 1
INACTIVE INGREDIENTS: PARAFFIN; LANOLIN; PHENOL

83124-003

Active Ingredient

Salicylic acid 40%

Purpose

Wart Remover

Use

For the removal of common warts. The common wart is easily recognized by the rough ‘cauliflower-like’ appearance of the surface.

Warnings

For external use only.

Do not use

on irritated, infected or reddened skin
on genital warts and warts on the face
on moles, birthmarks and warts with hair growing from them
on mucous membranes

When Using

Ask a doctor before use if you have
diabetes poor blood circulatio

Keep Oot Of Reach Of Children

If swallowed, get medical help or contact a Poison Control Center right away.

Directions

wash affected area: may soak wart in warm water for 5 minutes
dry area thoroughly
remove bandage strips by peeling backing off
If necessary, cut medicated patch to fit wart
carefully apply medicated plaster
repeat procedure every 48 hours as needed (until wart is removed) for up to 12 week

Other information

Store between 59° and 86°F (15° and 30°C).

Inactive ingredients

hard paraffin, lanolin, phenol

Questions

1-914-875-2018